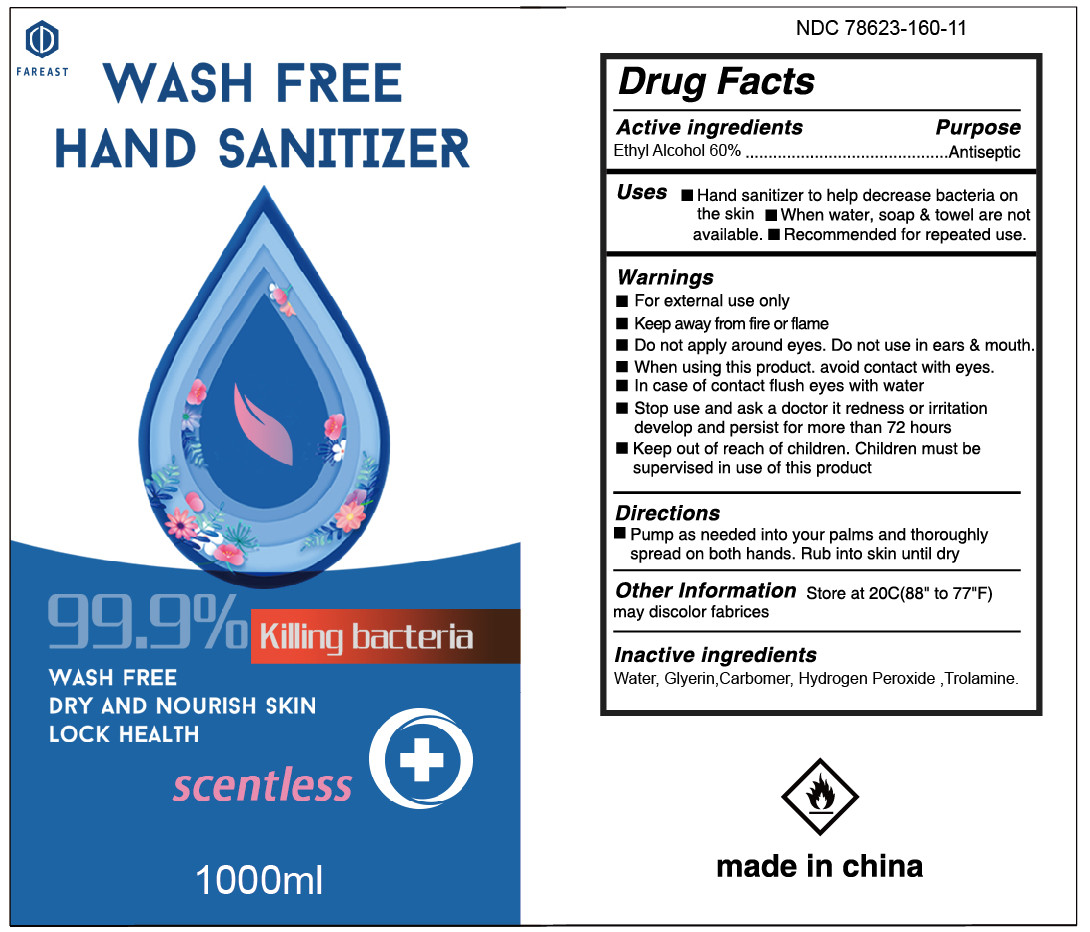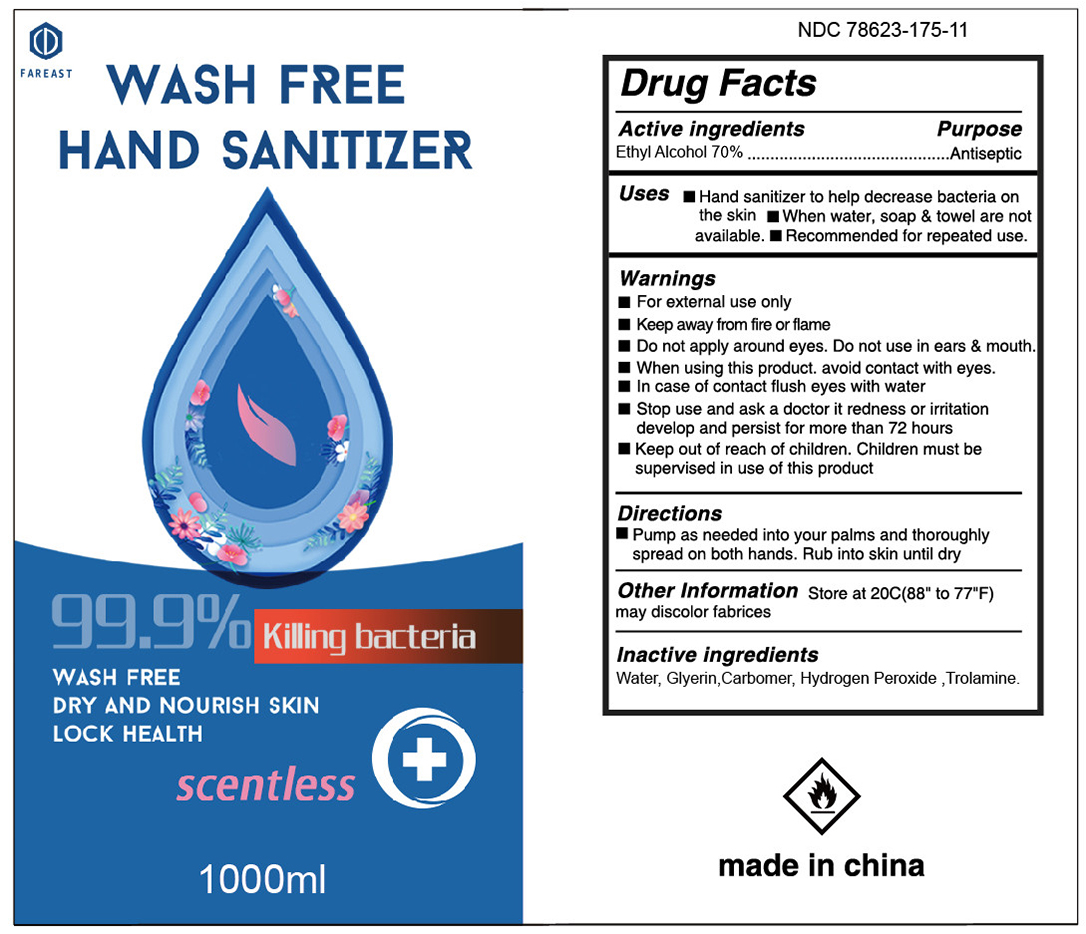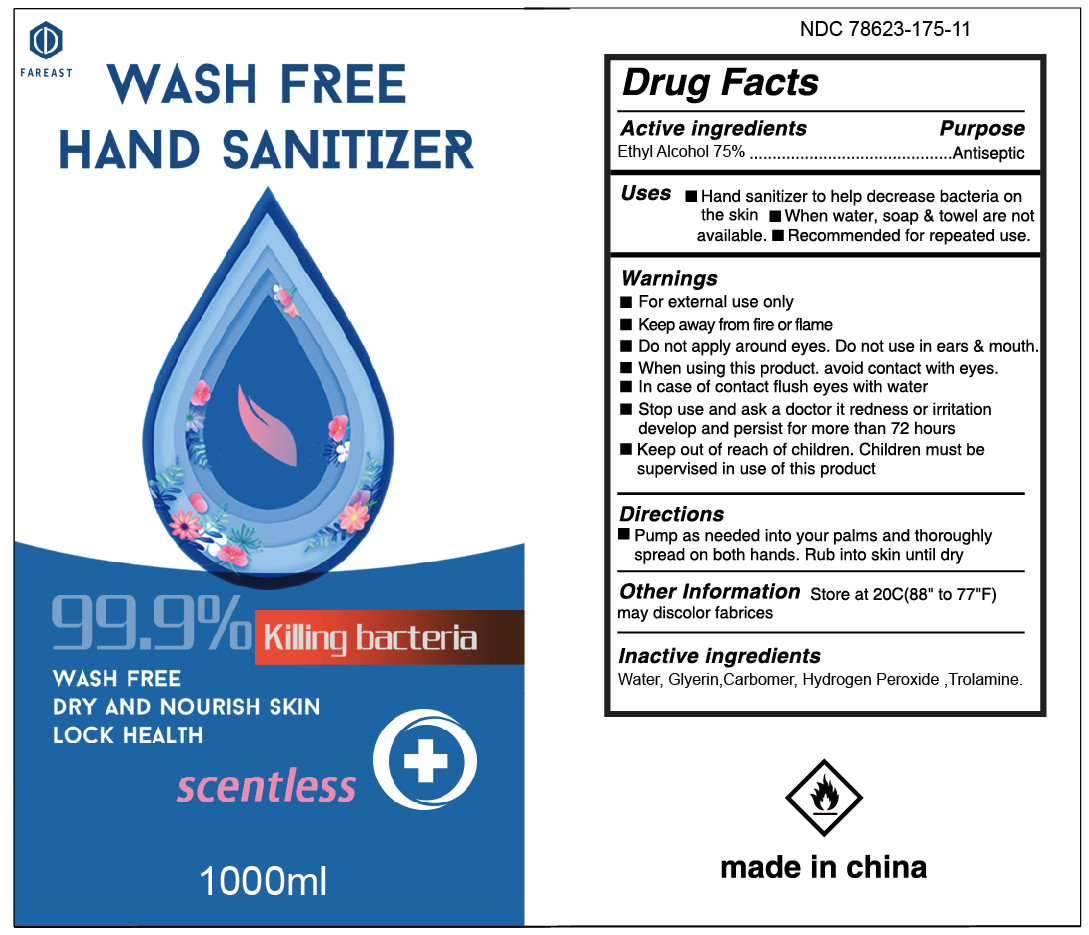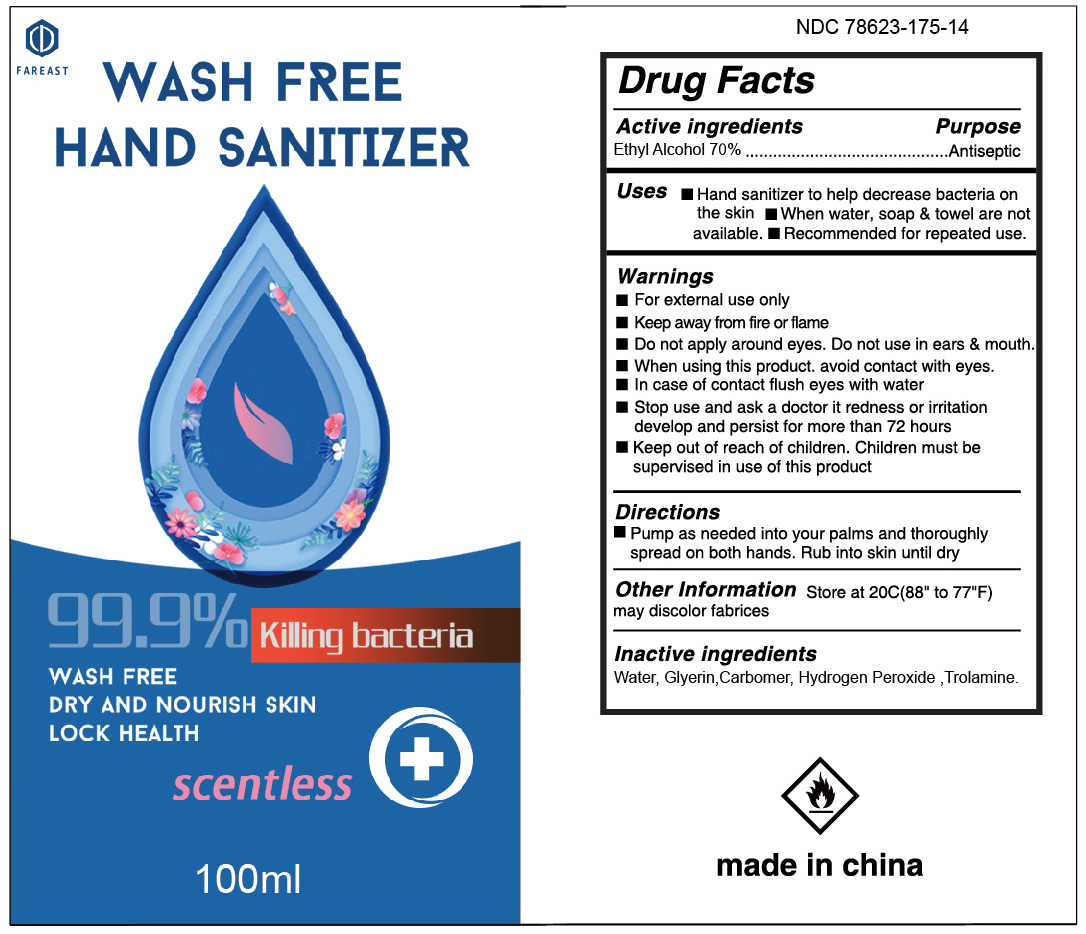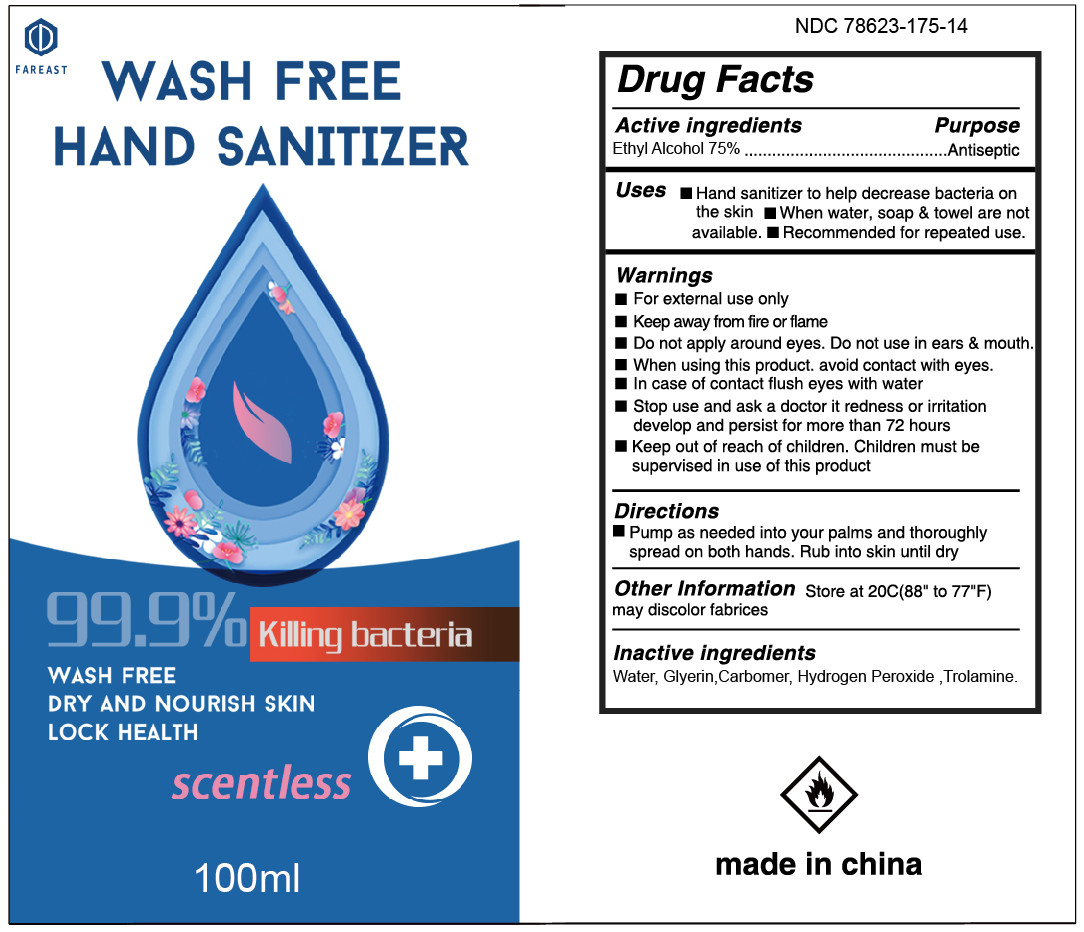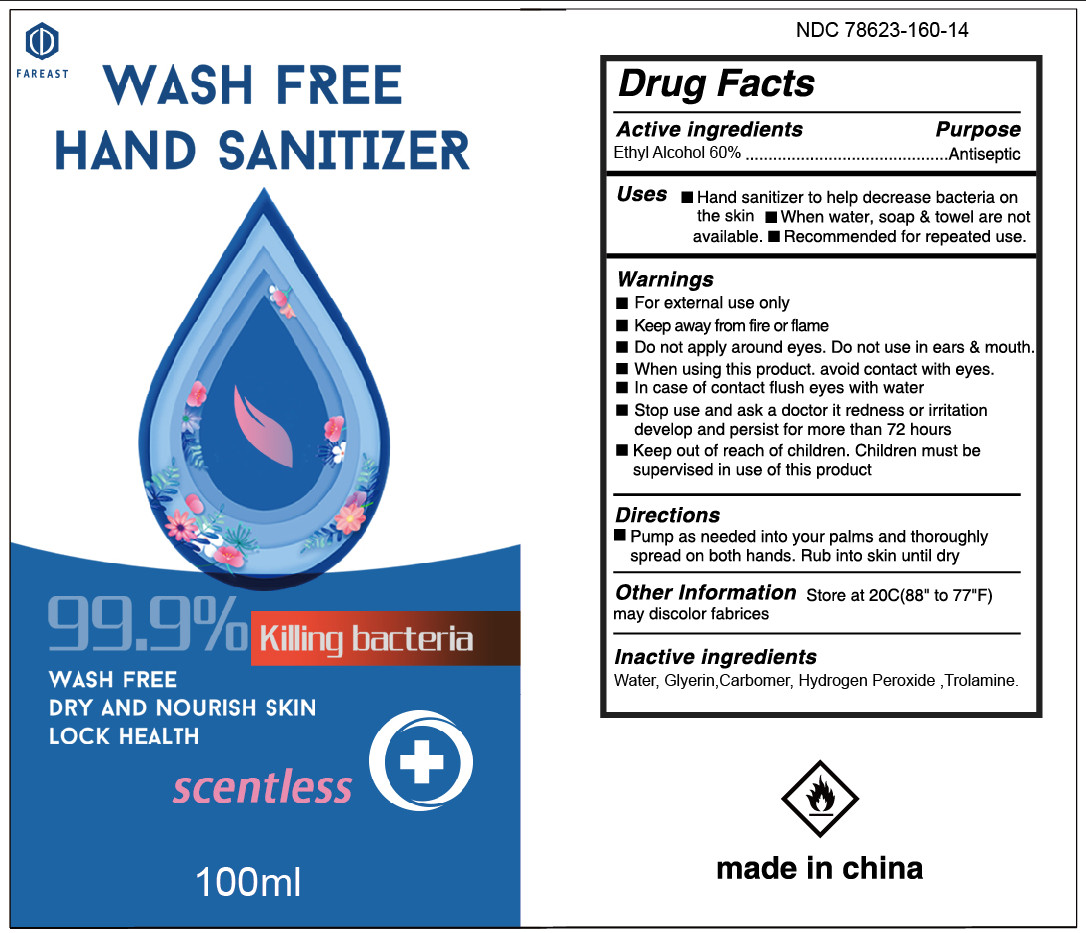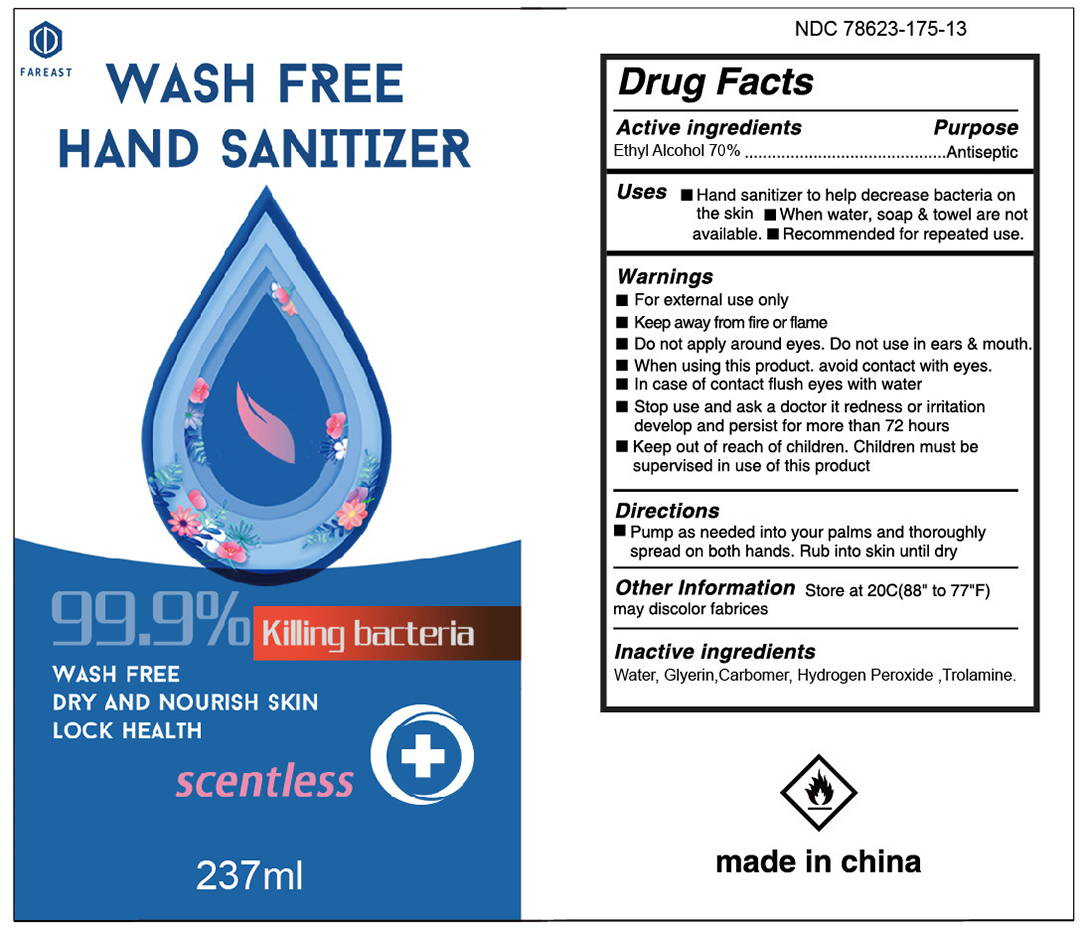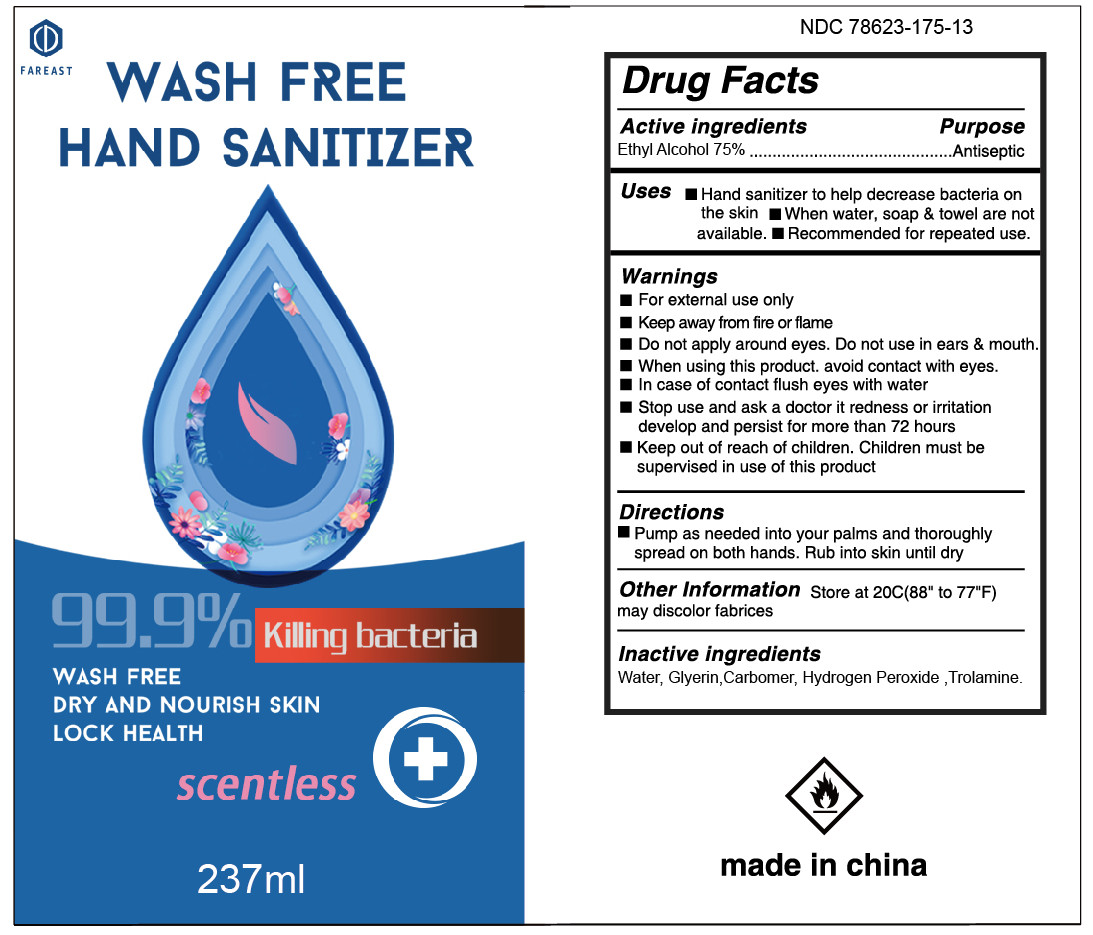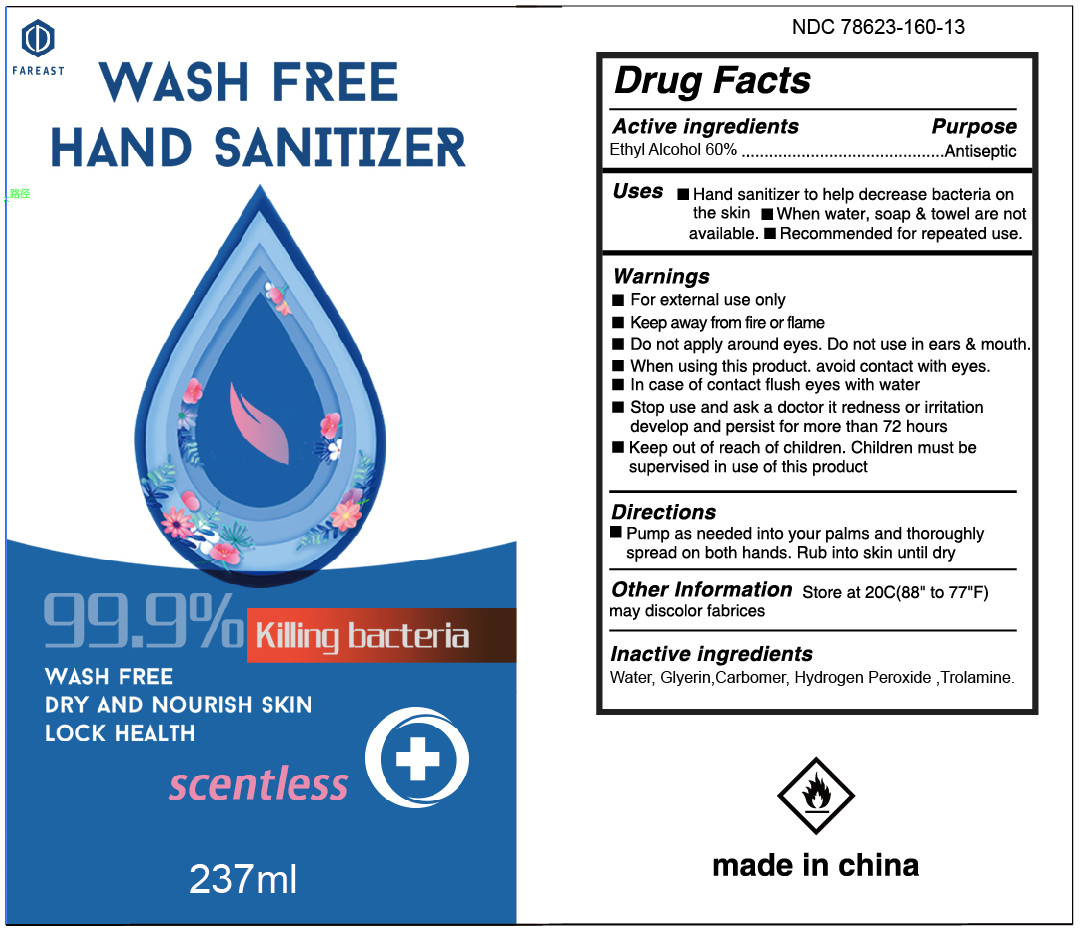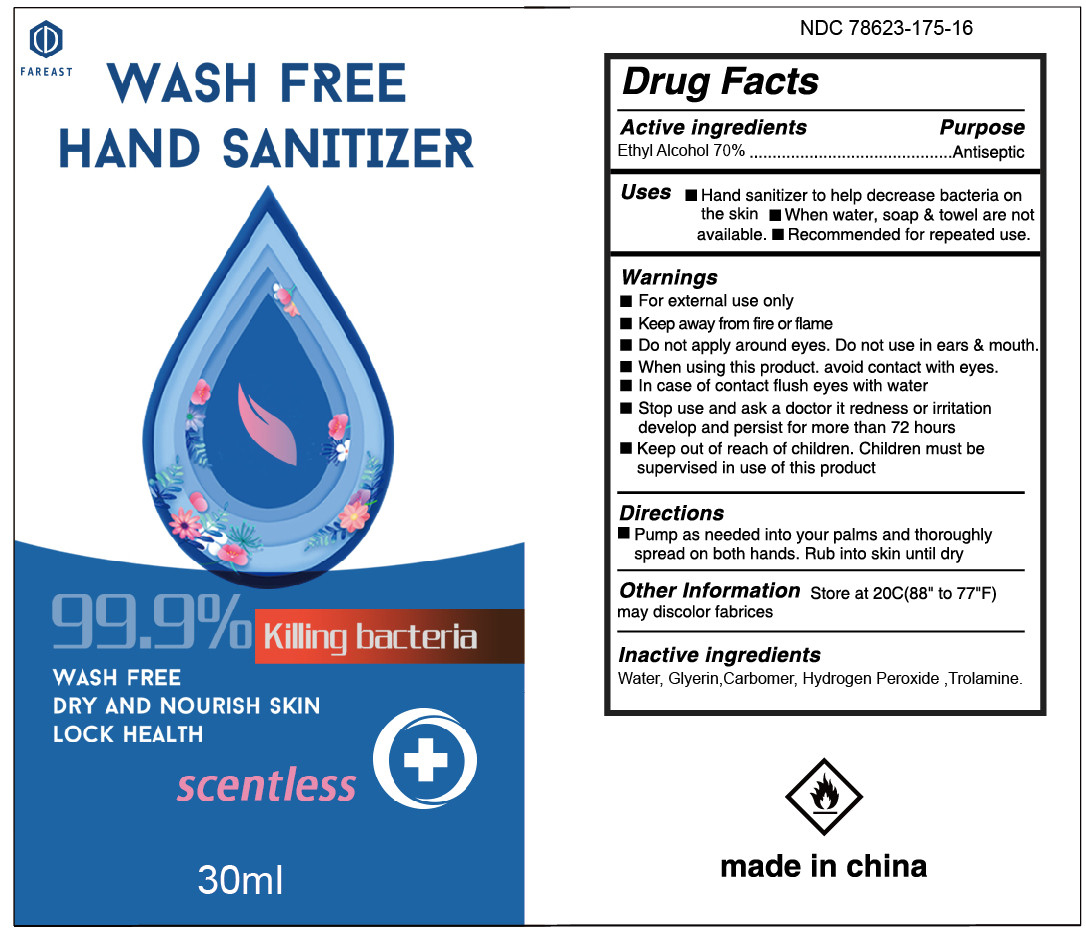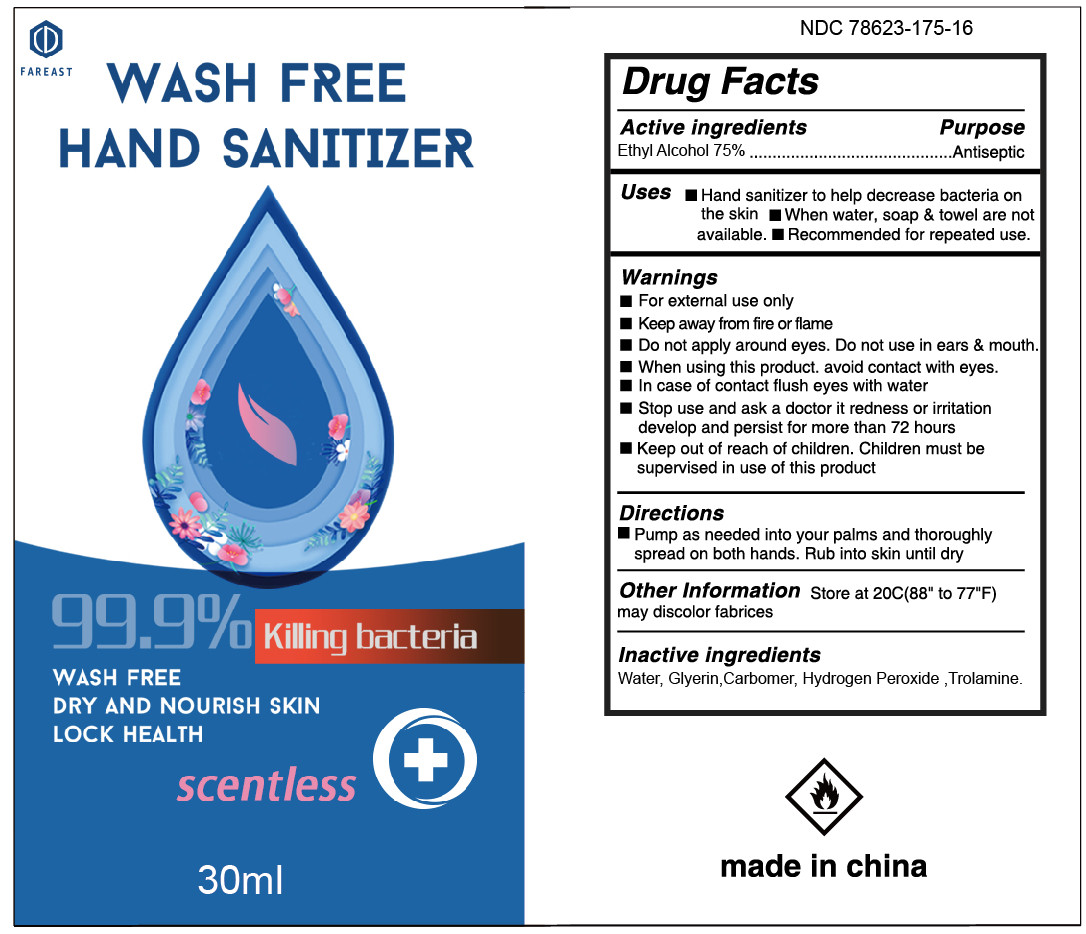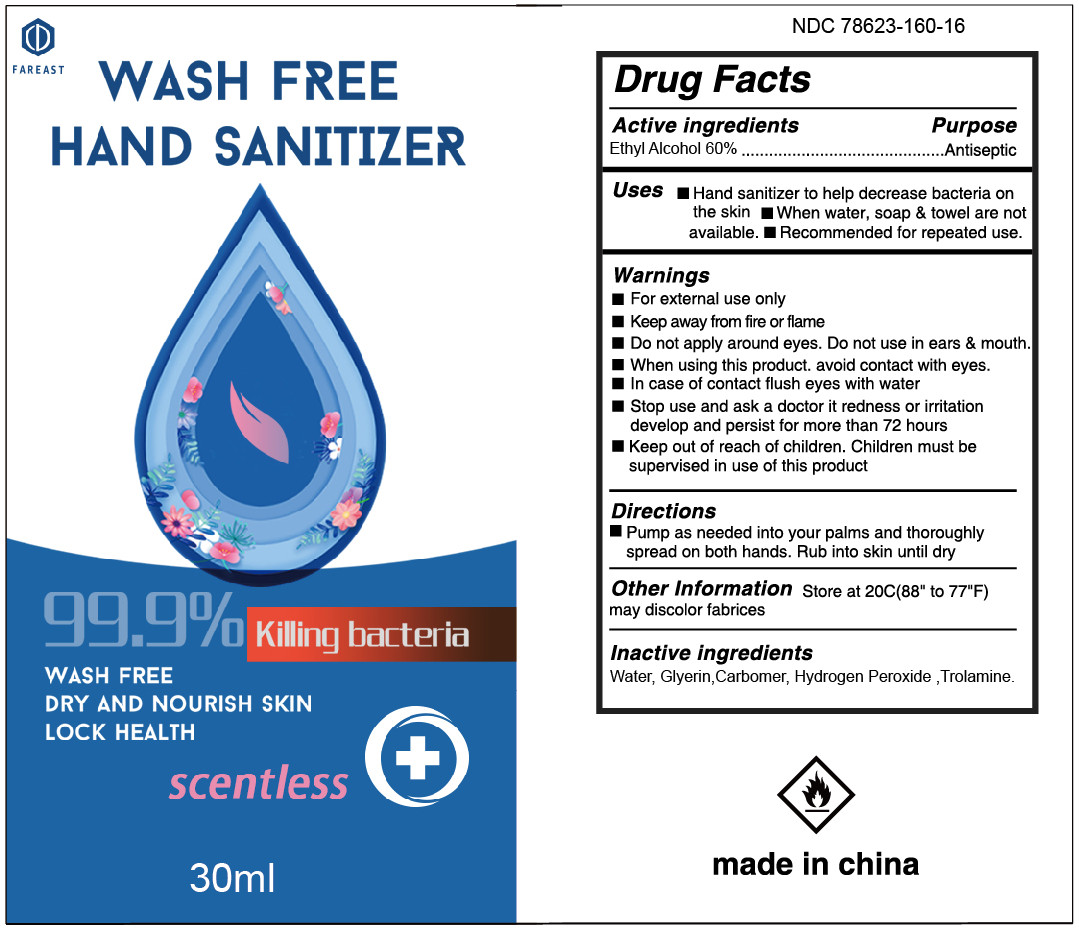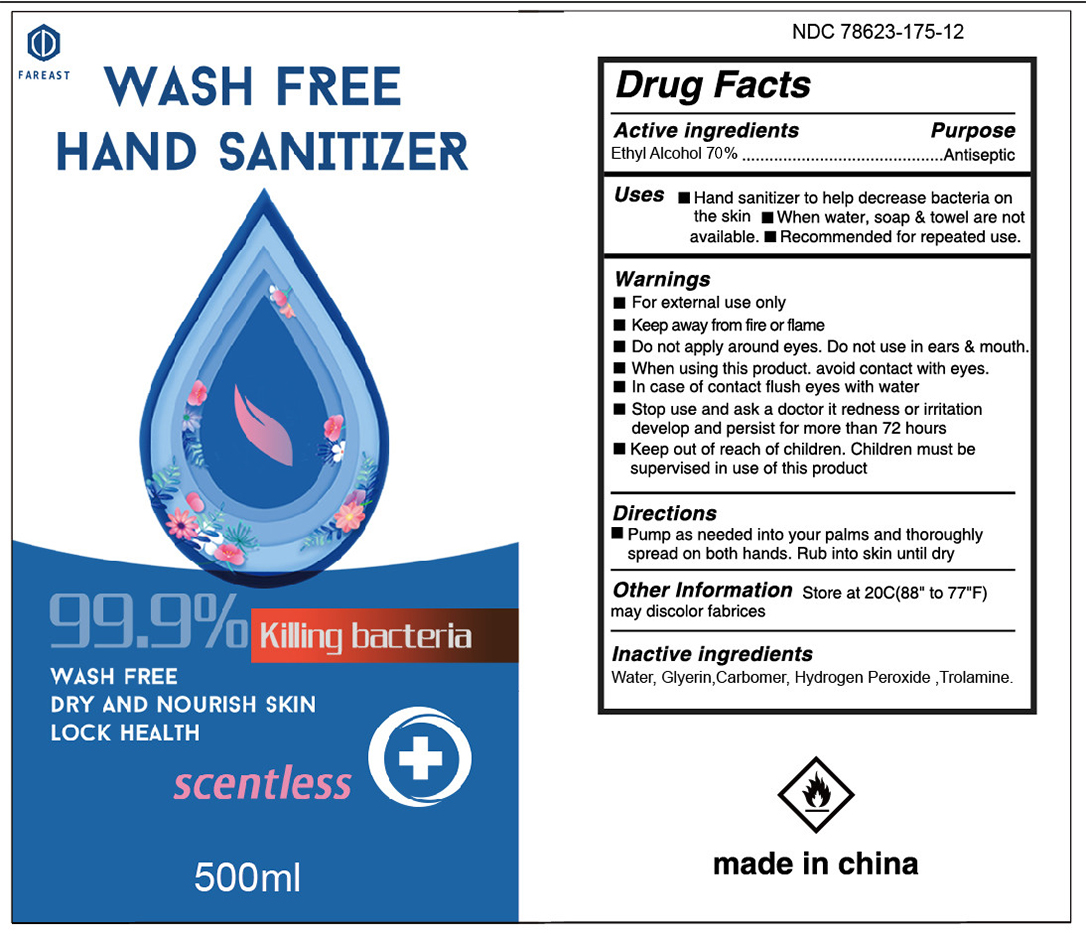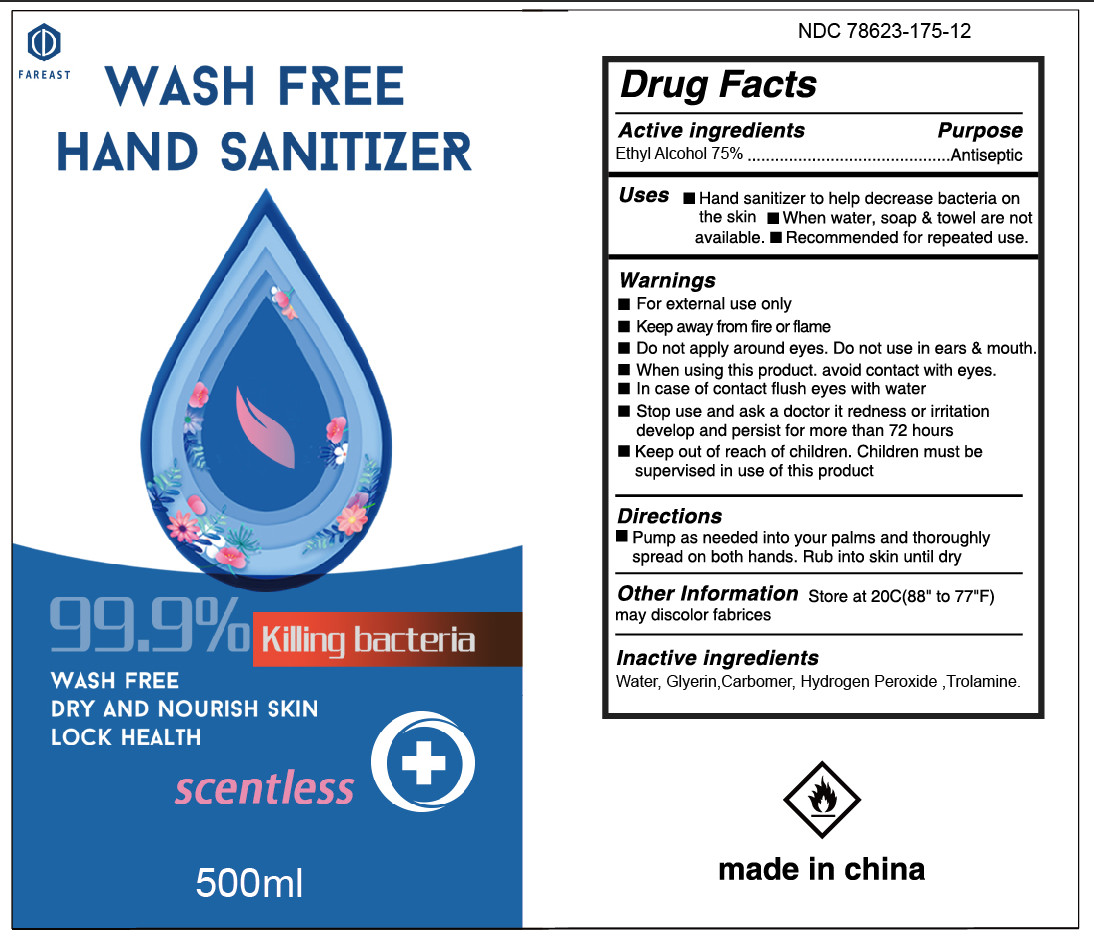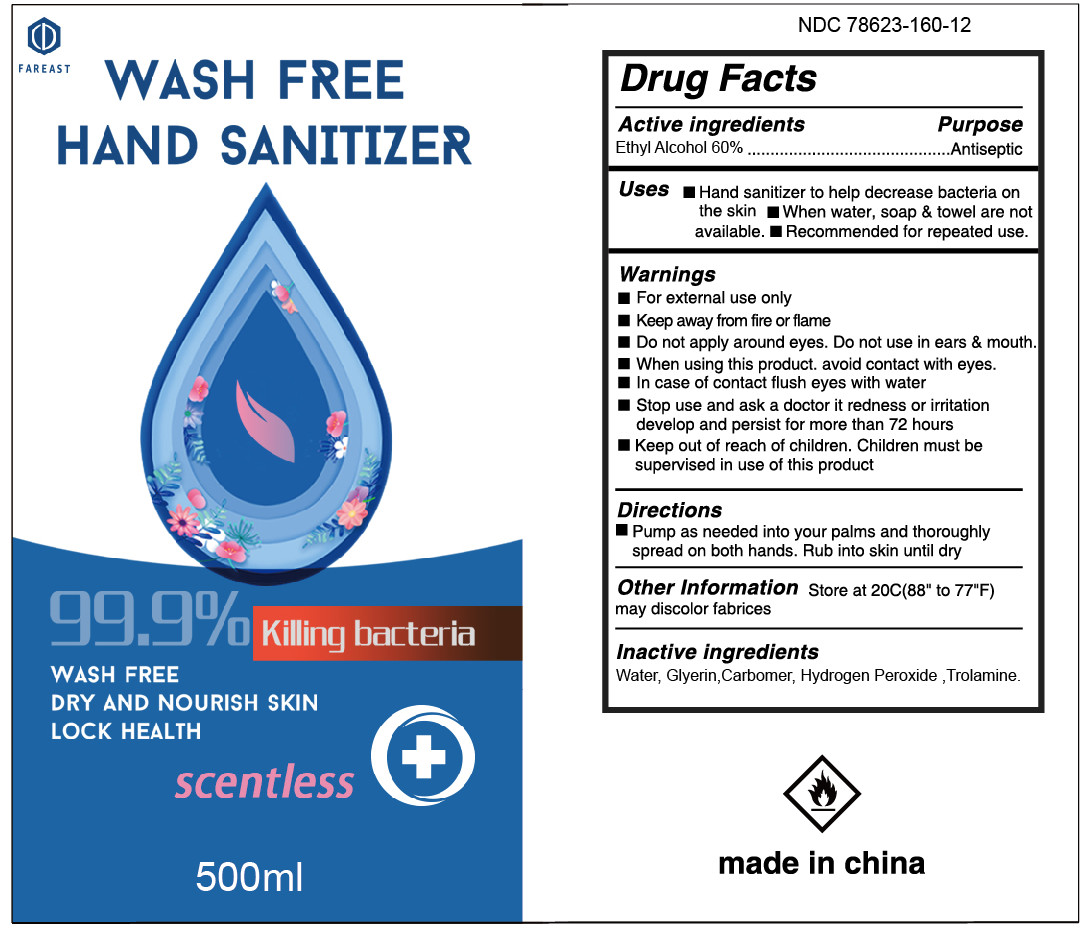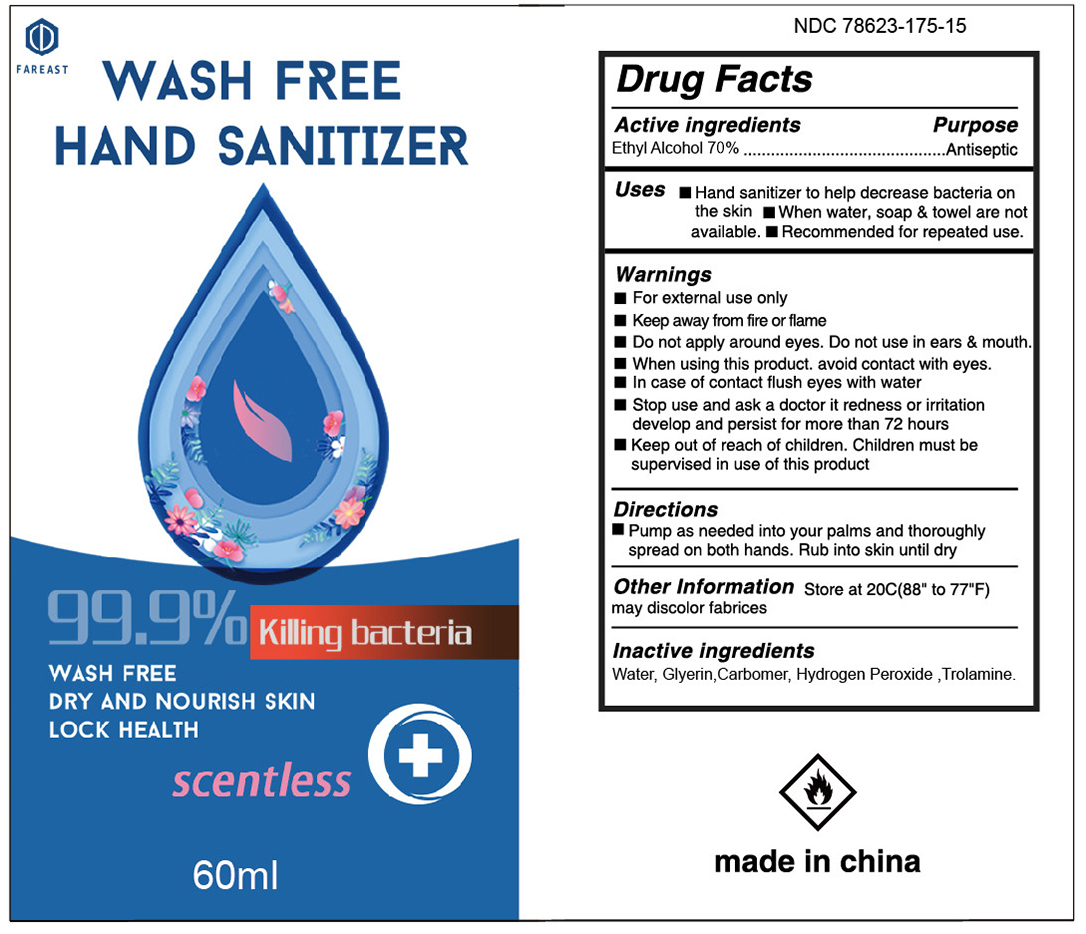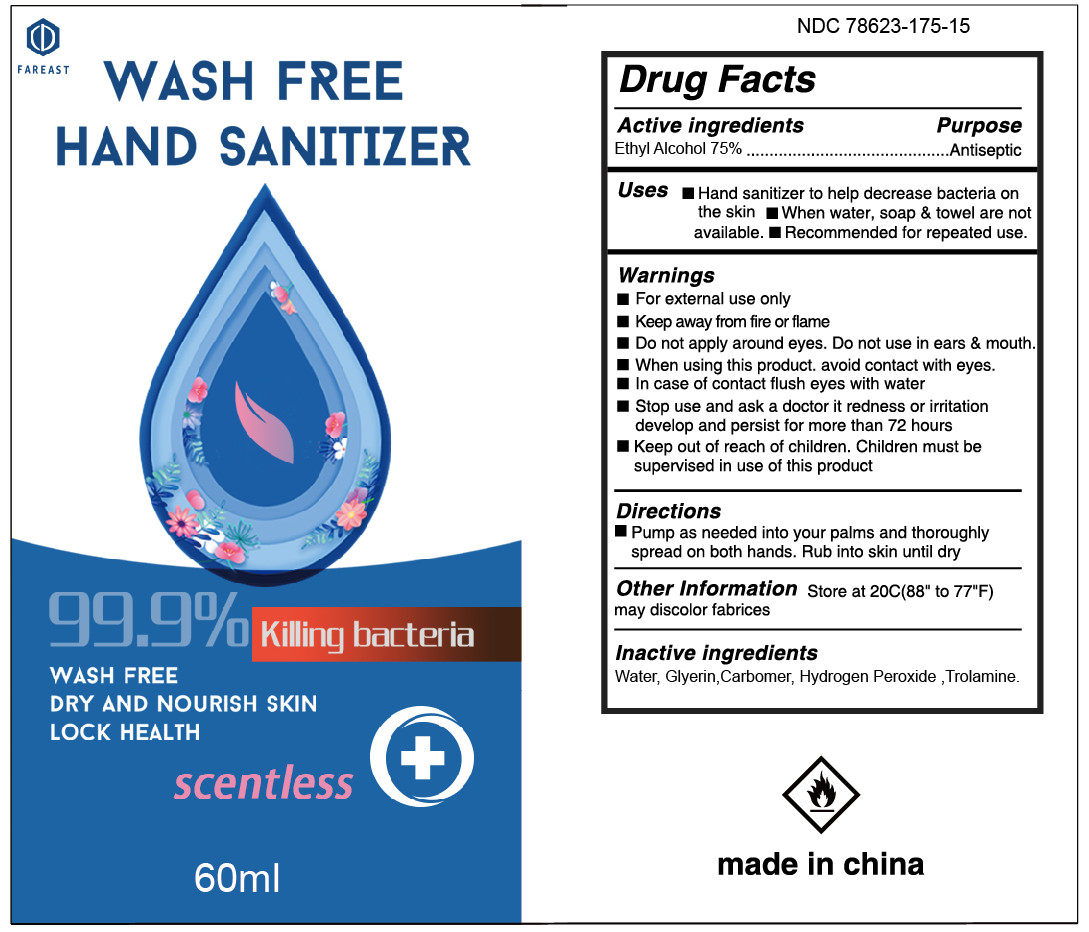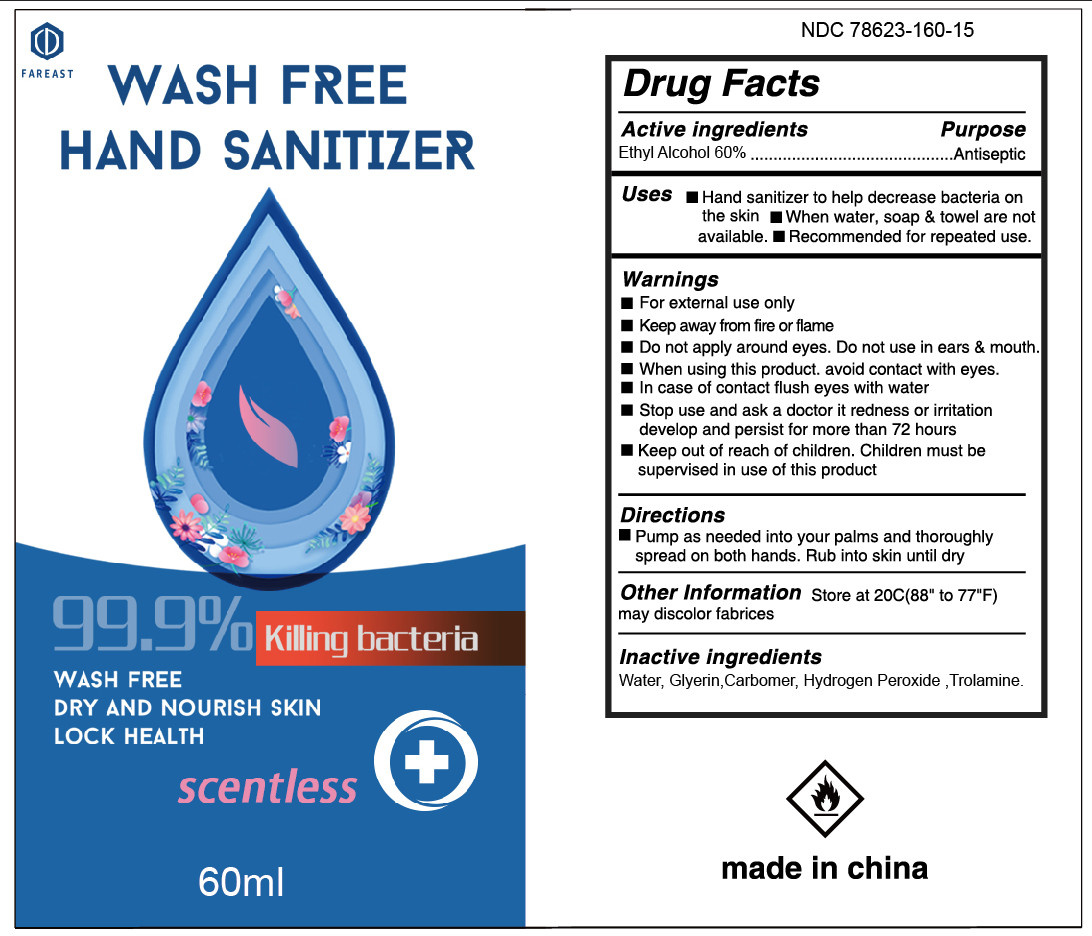 DRUG LABEL: Hand Sanitizer
NDC: 78623-370 | Form: GEL
Manufacturer: ningbo fareast industry co.,ltd
Category: otc | Type: HUMAN OTC DRUG LABEL
Date: 20210104

ACTIVE INGREDIENTS: ALCOHOL 70 mL/100 mL
INACTIVE INGREDIENTS: WATER; TROLAMINE; HYDROGEN PEROXIDE; GLYCERIN; CARBOXYPOLYMETHYLENE

ACTIVE INGREDIENT

alcohol 75% v/v purpose :antiseptic

alcohol 70% v/v purpose :antiseptic

alcohol 60% v/v purpose :antiseptic

INDICATIONS AND USAGE

to help reduce bacteria that potentially can cause disease.for use when soap and water are not available

WARNINGS

for external use only,flammable,keep away from heat or flame

DO NOT USE

. in children less than 2 months of age
.on open skin wounds

when using this product keep out of eyes,ears,and mouth in case of contact with eyes,rinse eyes thorough with water
stop use and ask a doctor if irritation or rash occurs,these may be signs of a serious condition.
keep out of reach of children,if swallowed,get medical help or contact a poison control center right away.

stop use and ask a doctor if irriation or rash occurs,these may be signs of a serious condition

keep out of reach of children ,if swallowed, get medical help or contact a posion control center right away

DOSAGE AND ADMINISTRATION

place enough product on hands to cover all surface,rub hands together until dry
supervise children under 6 years when using this product to avoid swallowing

package label principal display panel

75% alcohol concent

1000ml NDC: 78623-375-01

500ml NDC: 78623-375-02

237ml NDC: 78623-375-03

100ml NDC: 78623-375-04

60ml NDC: 78623-375-05

30ml NDC: 78623-375-06

70% alcohol concent

1000ml NDC: 78623-370-01

500ml NDC: 78623-370-02

237ml NDC: 78623-370-03

100ml NDC: 78623-370-04

60ml NDC: 78623-370-05

30ml NDC: 78623-370-06

60% alcohol concent

1000ml NDC: 78623-360-01

500ml NDC: 78623-360-02

237ml NDC: 78623-360-03

100ml NDC: 78623-360-04

60ml NDC: 78623-360-05

30ml NDC: 78623-360-06